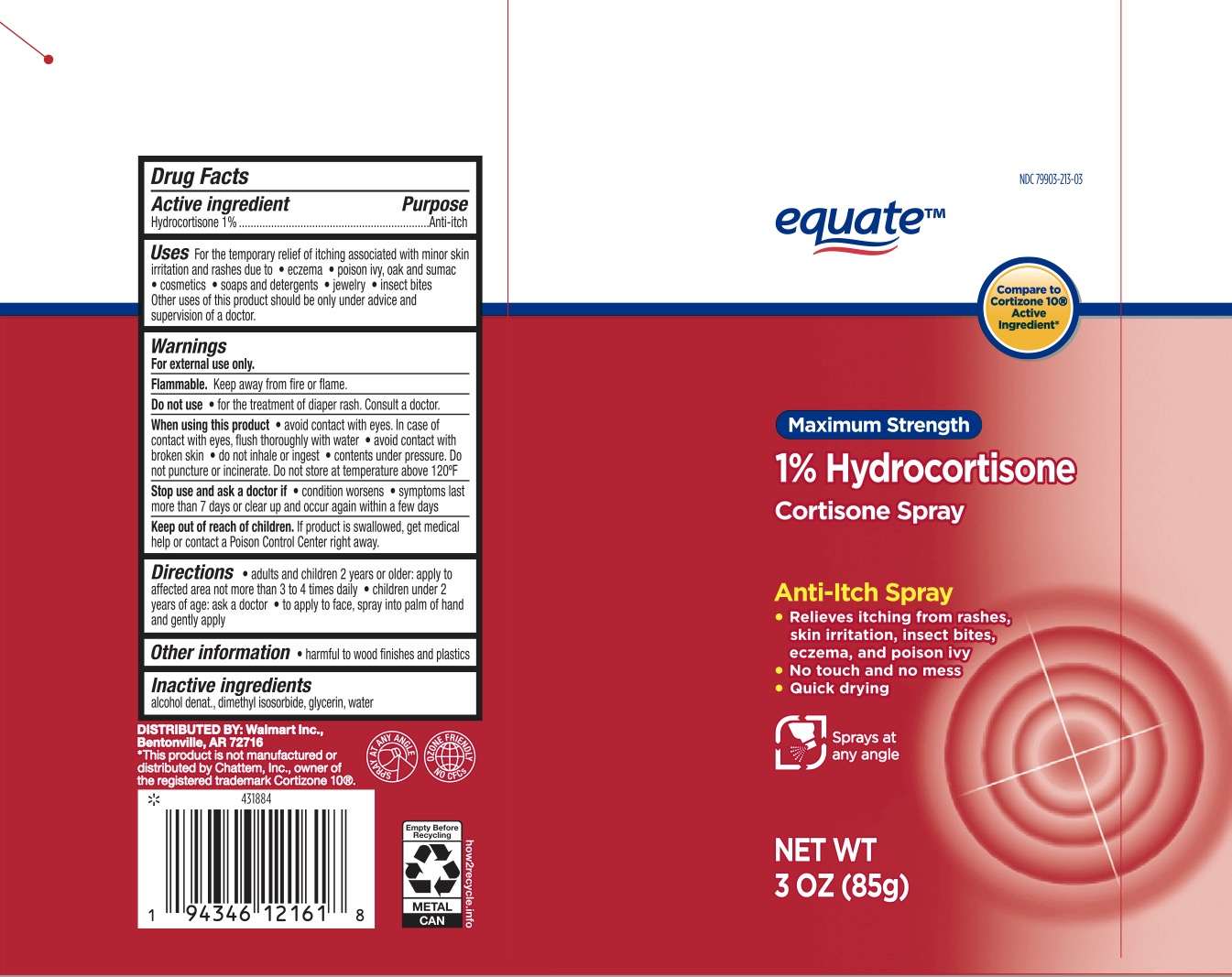 DRUG LABEL: Equate Cortisone
NDC: 79903-213 | Form: SPRAY
Manufacturer: Walmart Inc
Category: otc | Type: HUMAN OTC DRUG LABEL
Date: 20231227

ACTIVE INGREDIENTS: HYDROCORTISONE 1 g/100 g
INACTIVE INGREDIENTS: WATER; ALCOHOL; DIMETHYL ISOSORBIDE; GLYCERIN

ACTIVE INGREDIENT

Hydrocortisone 1%

PURPOSE

Anti-itch

INDICATIONS AND USAGE

For the temporary relief of itching associated with minor skin irritation and rashes due to

- eczema
- poison ivy, oak, and sumac
- cosmetics
- soaps and detergents
- jewelry
- insect bites

Other uses of this product should be only under advice and supervision of a doctor.

WARNINGS

For external use only.

Flammable. Keep away from fire or flame.

Do not use for the treatment of diaper rash. Consult a doctor.

When using this product

- avoid contact with eyes. In case of contact with eyes, flush thoroughly with water
- avoid contact with broken skin
- do not inhale or ingest
- contents under pressure. Do not puncture or incinerate. Do not store at temperature above 120F.

Stop use and ask a doctor if

condition worsens

symptoms last more than 7 days or clear up and occur again within a few days.

KEEP OUT OF REACH OF CHILDREN

If product is swallowed, get medical help or contact a Poison Control Center right away.

DOSAGE AND ADMINISTRATION

Adults and children 2 years or older: apply to affected area not more than 3 to 4 times daily

Children under 2 years of age: ask a doctor

To apply to face, spray into palm of hand and gently apply.

INACTIVE INGREDIENT

Alcohol denat., dimethyl isosorbide, glycerin, water.